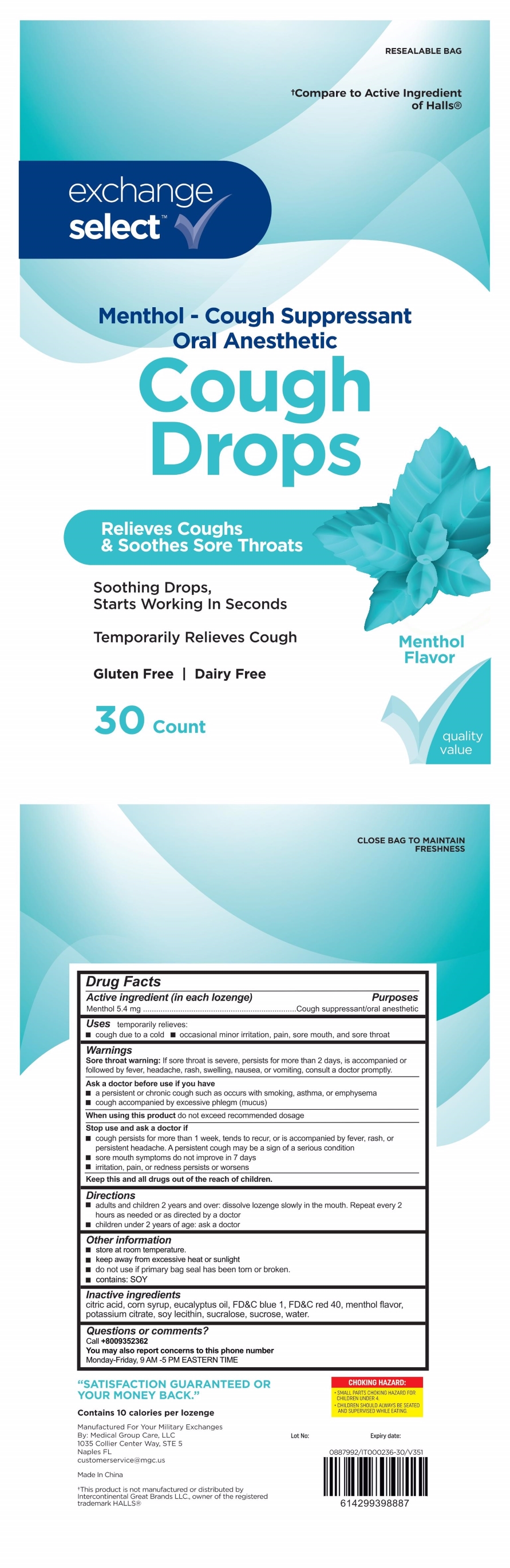 DRUG LABEL: Menthol Flavor Cough Drop
NDC: 83698-581 | Form: LOZENGE
Manufacturer: Xiamen Kang Zhongyuan Biotechnology Co., Ltd.
Category: otc | Type: HUMAN OTC DRUG LABEL
Date: 20251229

ACTIVE INGREDIENTS: MENTHOL 5.4 mg/1 1
INACTIVE INGREDIENTS: CITRIC ACID MONOHYDRATE; FD&C BLUE NO. 1; CORN SYRUP; EUCALYPTUS OIL; LECITHIN, SOYBEAN; SUCRALOSE; SUCROSE; WATER; FD&C RED NO. 40; POTASSIUM CITRATE

AAFES Menthol Cough Drop, Menthol 5.4 mg

Active ingredeint (in each Lozenge)

Menthol 5.4 mg

Purpose

Cough suppressant/Oral anesthetic

Uses

temporarily relieves:

- cough due to a cold
- occasional minor irritation, pain, sore mouth, and sore throat

Warnings

Sore throat warning:If sore throat is severe, persists for more than 2 days, is accompanied or followed by fever, headache, rash, swelling, nausea, or vomiting, consult a doctor promptly.

Ask a doctor before use if you have

- persistent or chronic cough such as occurs with smoking, asthma, or emphysema
- cough accompanied by excessive phlegm (mucus)

When using this product do not exceed recommended dosage

Stop use and ask doctor if

- cough persists for more than 1 week, tends to recur, or is accompanied by fever, rash, or persistent headache. A persistent cough may be a sign of a serious condition.
- sore mouth does not improve in 7 days
- irritation, pain or redness persists or worsens

Keep out of reach of children.

Directions

- adults and children 2 years and over: dissolve lozenge slowly in mouth. Repeat every 2 hours as needed or as directed by a doctor.
- children under 2 years: ask a doctor

Other information

- Store at room termperature
- keep away from excessive heat or sunlight
- do not use if primary bag seal has been torn or broken
- CONTAINS: SOY

Inactive ingredients

citric acid, corn syrup, eucalyptus oil, FD&C blue 1, FD&C red 40, menthol flavor, potassium citrate, soy lecithin, sucralose, sucrose, water

Questions or comments?

Call +8009352362

You may also report concerns to this phone number

Monday-Friday, 9AM - 5PM Eastern Time